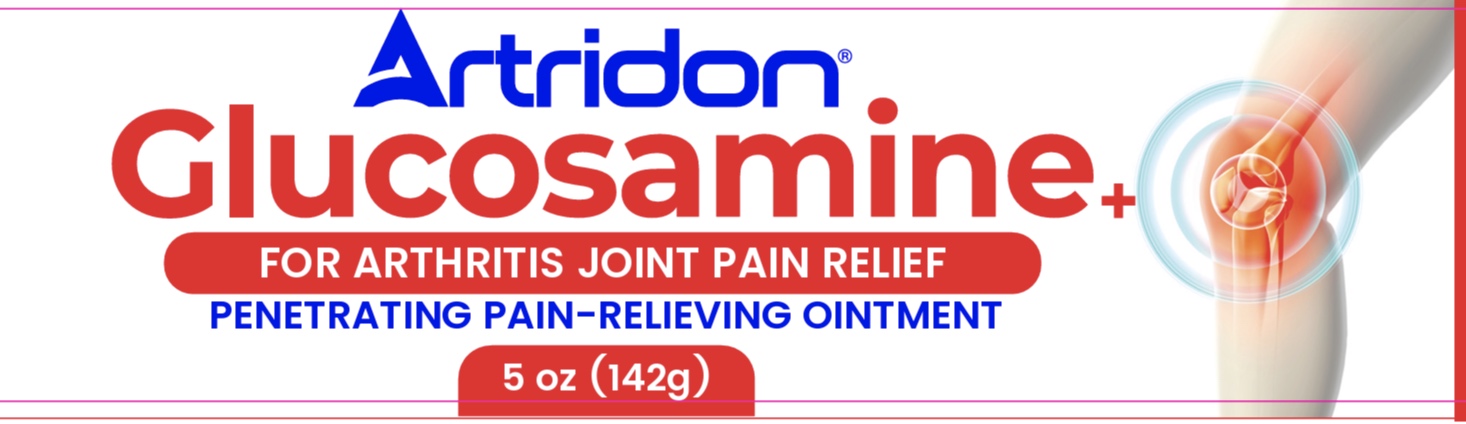 DRUG LABEL: Artridon
NDC: 55758-030 | Form: OINTMENT
Manufacturer: Pharmadel LLC
Category: otc | Type: HUMAN OTC DRUG LABEL
Date: 20260107

ACTIVE INGREDIENTS: MENTHOL, UNSPECIFIED FORM 2 g/100 g; METHYL SALICYLATE 15 g/100 g
INACTIVE INGREDIENTS: MINERAL OIL; CLOVE OIL; POTASSIUM HYDROXIDE; DIMETHICONE; GLYCERYL MONOSTEARATE; ISOPROPYL MYRISTATE; WATER; PHENOXYETHANOL; GLUCOSAMINE HYDROCHLORIDE; STEARIC ACID; TRIETHYLENE GLYCOL; GLYCERIN; CETYL ALCOHOL

Artridon Glucosamine (DIL)

Active Ingredients and Purpose

Active ingredients | Purpose
Menthol 2%............................... | Topical analgesic
Methyl Salicylate 15% ............... | Topical analgesic

Uses

For the temporary relief of minor aches and pains of muscles and joints associated with

- simple backaches
- arthritis
- strains
- bruises
- sprains

Warnings

For external use only. Avoid contact with the eyes.

When using this product

- do not apply on wounds or damaged skin
- do not bandage tightly

Stop use and ask a doctor if

- condition worsens
- symptoms persist for more than 7 days or clear up and occur again within a few days

If pregnant or breast-feeding,

ask a health professional before use.

Keep out of reach of children.

If swallowed, get medical help, or contact a Poison Control Center immediately.

Directions

- adults and children 12 years of age and older: apply to affected area not more than 3 to 4 times daily
- children under 12 years of age: do not use, consult a doctor

Other information

- store between 68-77°F (20-25°C)
- don’t use if foil seal under cap is broken, torn, or missing

Inactive ingredients

cetyl alcohol, clove oil, dimethicone, glucosamine hydrochloride, glycerin, glyceryl monostearate, isopropyl myristate, mineral oil, phenoxyethanol, potassium hydroxide, stearic acid, triethylene glycol, water

Dist. by/por:

Pharmadel LLC

New Castle, DE, 19720

Questions? +1-866-359-3478

Made in India/ Hecho en India